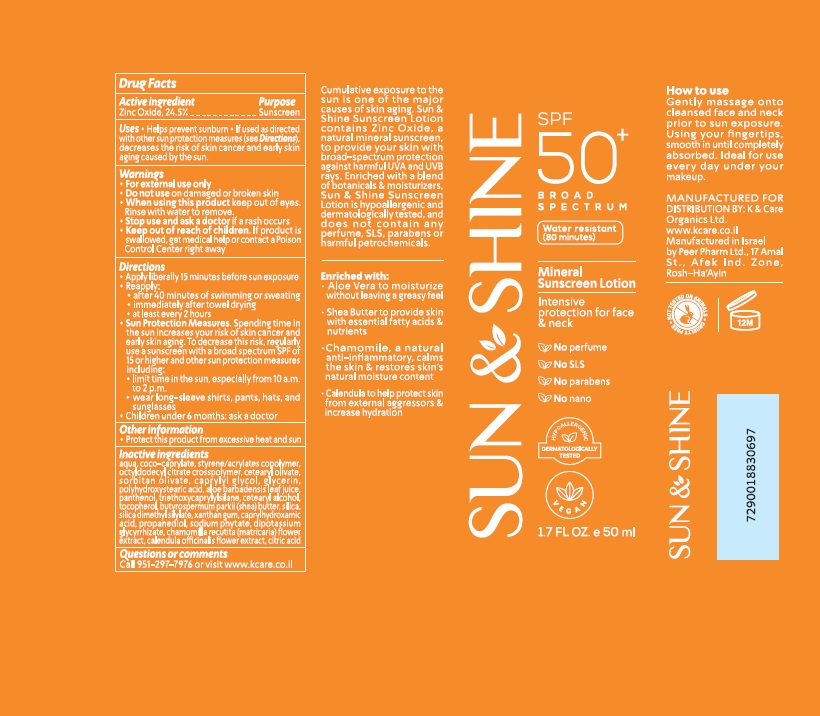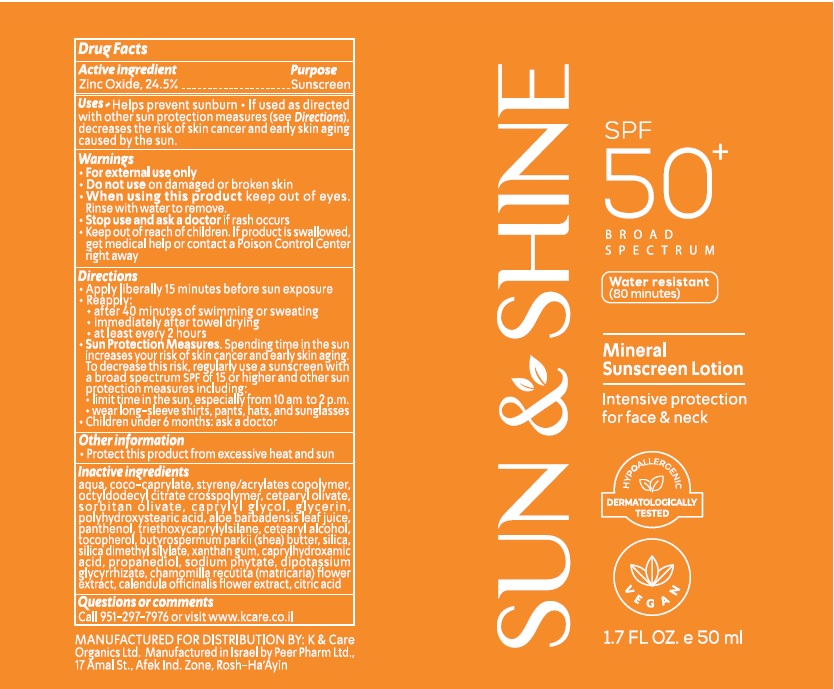 DRUG LABEL: SUN and SHINE MINERAL SUNSCREEN
NDC: 69435-1505 | Form: CREAM
Manufacturer: Peer Pharm Ltd.
Category: otc | Type: HUMAN OTC DRUG LABEL
Date: 20260112

ACTIVE INGREDIENTS: ZINC OXIDE 24.5 g/100 mL
INACTIVE INGREDIENTS: WATER; 1-(ETHYLTRISULFANYL)PROPANE; TRIOCTYLDODECYL CITRATE; ACRYLATES CROSSPOLYMER-4; CETEARYL OLIVATE; SORBITAN OLIVATE; ISOBUTANE; CASTOR OIL; GLYCERIN; PROPANEDIOL 1-PHOSPHATE; CHAMOMILE; PANTHENOL; ALOE; 1,4-BUTANEDITHIOL; TOCOPHEROL; CETEARYL ETHYLHEXANOATE; HEXASODIUM PHYTATE; CALENDULA OFFICINALIS SEED OIL; TRIETHOXYCAPRYLYLSILANE; SHEA BUTTER; SILICA DIMETHYL SILYLATE; XANTHAN GUM; CAPRYLHYDROXAMIC ACID; DIPOTASSIUM GLUCOSE-6-PHOSPHATE; POLYHYDROXYSTEARIC ACID (2300 MW); CAPRYLYL GLYCOL; COCO-CAPRYLATE; SODIUM ACRYLATE/STYRENE SULFONATE COPOLYMER (11000 MW)

Sun and Shine Mineral Sunscreen Lotion SPF 50. Intensive Protection for face & neck

Active Ingredients

Zinc Oxide 24.5%

Purpose

Sunscreen

Uses

- Helps prevent sunburn
- if used as directed with other sun protection measures (see Directions), decreases the risk of skin cancer and early skin aging caused by the sun.

Warnings

- For external use only
- Do not use on damaged or broken skin.
- When using this product, Keep out of eyes. Rinse with water to remove.
- Stop use and ask a doctor if rash or irritation develops and lasts.

Keep out of reach of children.

If swallowed, call a poison control center or get medical help right away.

Directions

Apply liberally 15 minutes before sun exposure
• Reapply:
• after 40 minutes of swimming or sweating
• immediately after towel drying
• at least every 2 hours
• Sun Protection Measures.Spending time in the sun increases your risk of skin cancer and early skin aging. To decrease this risk, regularly use a sunscreen with a broad-spectrum SPF of 15 or higher and other sun protection measures including:
• limit time in the sun, especially from 10 am to 2 p.m.
• wear long-sleeve shirts, pants, hats, and sunglasses
• Children under 6 months: ask a doctor

Other information

protect this product from excessive heat and sun

Inactive Ingredients

aqua, coco-caprylate, styrene/acrylates copolymer, octyldodecyl citrate crosspolymer, cetearyl olivate, sorbitan olivate, caprylyl glycol, glycerin, polyhydroxystearic acid, aloe barbadensis leaf juice, panthenol, triethoxycaprylylsilane, cetearyl alcohol, tocopherol, butyrospermum parkii (shea) butter, silica, silica dimethyl silylate, xanthan gum, caprylhydroxamic acid, propanediol, sodium phytate, dipotassium glycyrrhizate, chamomilla recutita (matricaria) flower extract, calendula officinalis flower extract, citric acid

Questions or Comments

Call 951-297-7976 or visit www.kcare.co.il